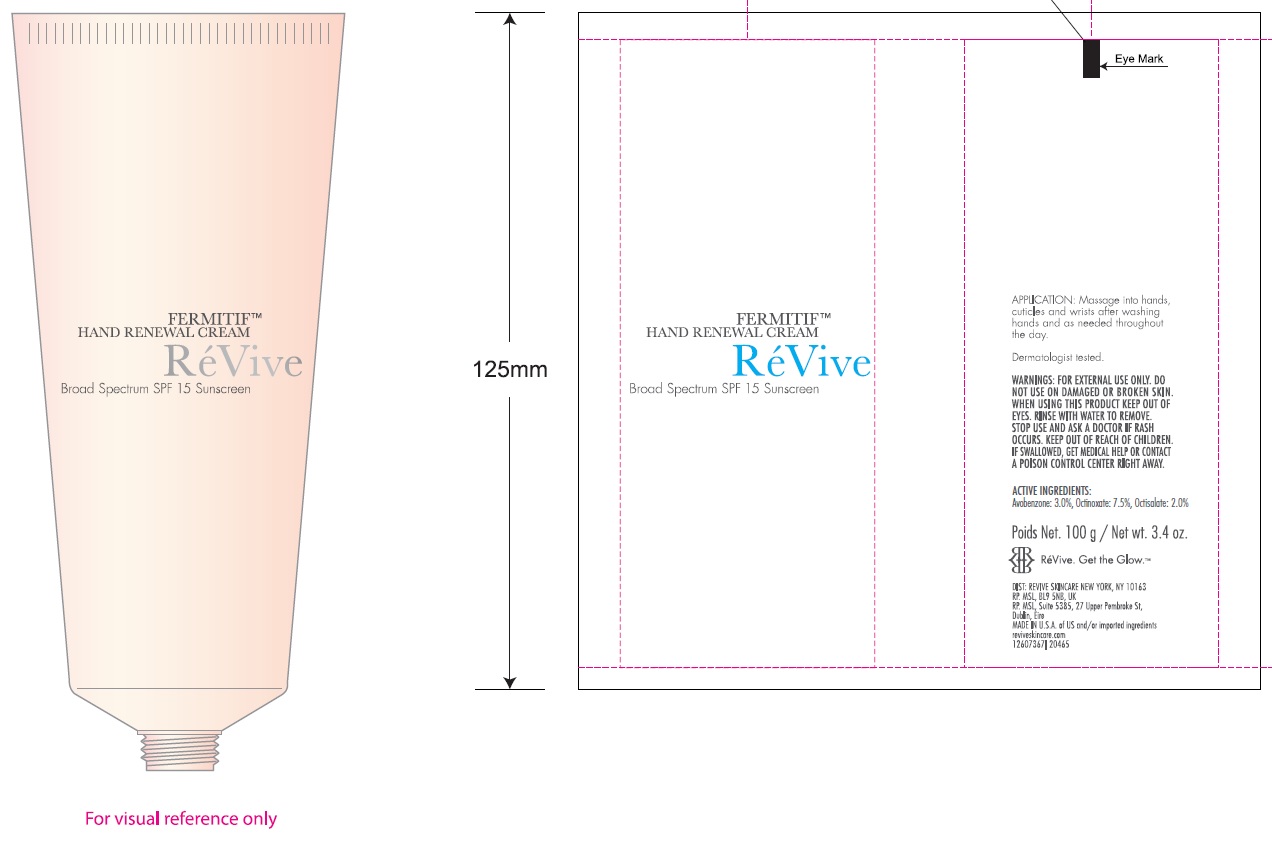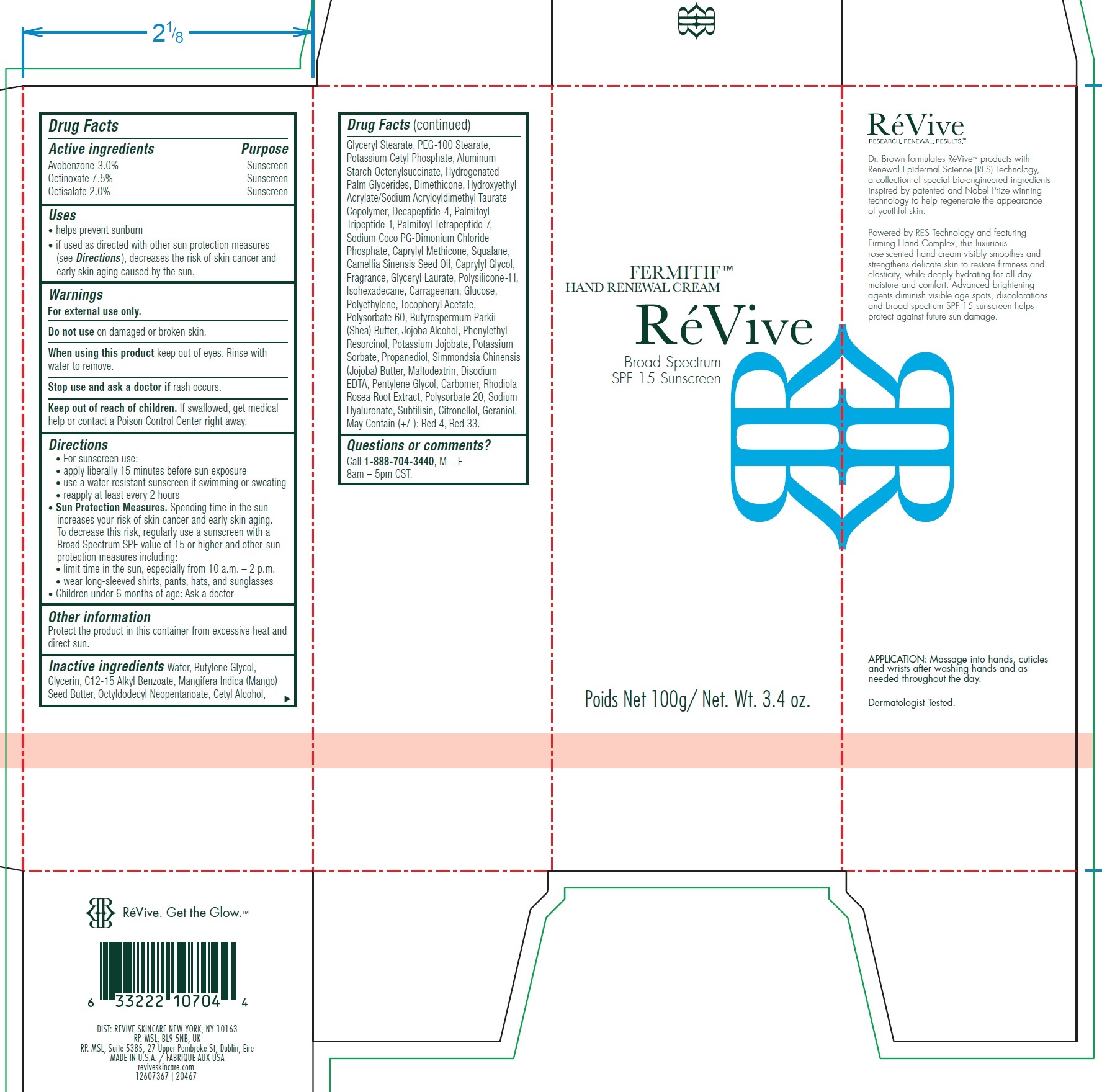 DRUG LABEL: Fermitif Hand Renewal Cream Broad Spectrum SPF 15 Sunscreen
NDC: 82691-148 | Form: CREAM
Manufacturer: RV Skincare LLC
Category: otc | Type: HUMAN OTC DRUG LABEL
Date: 20231106

ACTIVE INGREDIENTS: AVOBENZONE 30 mg/1 g; OCTINOXATE 75 mg/1 g; OCTISALATE 20 mg/1 g
INACTIVE INGREDIENTS: ANHYDROUS DEXTROSE; HIGH DENSITY POLYETHYLENE; .ALPHA.-TOCOPHEROL ACETATE; POLYSORBATE 60; SHEA BUTTER; PHENYLETHYL RESORCINOL; POTASSIUM SORBATE; PROPANEDIOL; JOJOBA BUTTER; MALTODEXTRIN; EDETATE DISODIUM ANHYDROUS; PENTYLENE GLYCOL; CARBOMER HOMOPOLYMER, UNSPECIFIED TYPE; SEDUM ROSEUM ROOT; POLYSORBATE 20; HYALURONATE SODIUM; SUBTILISIN; .BETA.-CITRONELLOL, (R)-; GERANIOL; CAPRYLYL TRISILOXANE; SQUALANE; CAMELLIA SINENSIS SEED OIL; CAPRYLYL GLYCOL; GLYCERYL LAURATE; DIMETHICONE/VINYL DIMETHICONE CROSSPOLYMER (SOFT PARTICLE); ISOHEXADECANE; CARRAGEENAN; WATER; BUTYLENE GLYCOL; GLYCERIN; ALKYL (C12-15) BENZOATE; MANGIFERA INDICA SEED BUTTER; OCTYLDODECYL NEOPENTANOATE; CETYL ALCOHOL; GLYCERYL MONOSTEARATE; PEG-100 STEARATE; POTASSIUM CETYL PHOSPHATE; ALUMINUM STARCH OCTENYLSUCCINATE; HYDROGENATED PALM GLYCERIDES; DIMETHICONE; PALMITOYL TRIPEPTIDE-1; PALMITOYL TETRAPEPTIDE-7

Fermitif Hand Renewal Cream Broad Spectrum SPF 15 Sunscreen

Active ingredients

Avobenzone 3.0% Octinoxate 7.5% Octisalate 2.0%

Purpose

Sunscreen

Uses

- helps prevent sunburn
- if used as directed with other sun protection measures (see Directions), decreases the risk of skin cancer and early skin aging caused by the sun.

Warnings

For external use only.

Do not use

on damaged or broken skin.

When using this product

keep out of eyes. Rinse with water to remove.

Stop use and ask a doctor if

rash occurs.

Keep out of reach of children.

If swallowed, get medical help or contact a Poison Control Center right away.

Directions

- For sunscreen use:
- apply liberally 15 minutes before sun exposure
- use a water resistant sunscreen if swimming or sweating
- reapply at least every 2 hours
- Spending time in the sun increases your risk of skin cancer and early skin aging. To decrease this risk, regularly use a sunscreen with a Broad Spectrum SPF value of 15 or higher and other sun protection measures including: Sun Protection Measures.
- limit time in the sun, especially from 10 a.m. – 2 p.m.
- wear long-sleeved shirts, pants, hats, and sunglasses
- Children under 6 months of age: Ask a doctor

Other information

Protect the product in this container from excessive heat and direct sun.

Inactive ingredients

Water, Butylene Glycol, Glycerin, C12-15 Alkyl Benzoate, Mangifera Indica (Mango) Seed Butter, Octyldodecyl Neopentanoate, Cetyl Alcohol, Glyceryl Stearate, PEG-100 Stearate, Potassium Cetyl Phosphate, Aluminum Starch Octenylsuccinate, Hydrogenated Palm Glycerides, Dimethicone, Hydroxyethyl Acrylate/Sodium Acryloyldimethyl Taurate Copolymer, Decapeptide-4, Palmitoyl Tripeptide-1, Palmitoyl Tetrapeptide-7, Sodium Coco PG-Dimonium Chloride Phosphate, Caprylyl Methicone, Squalane, Camellia Sinensis Seed Oil, Caprylyl Glycol, Fragrance, Glyceryl Laurate, Polysilicone-11, Isohexadecane, Carrageenan, Glucose, Polyethylene, Tocopheryl Acetate, Polysorbate 60, Butyrospermum Parkii (Shea) Butter, Jojoba Alcohol, Phenylethyl Resorcinol, Potassium Jojobate, Potassium Sorbate, Propanediol, Simmondsia Chinensis (Jojoba) Butter, Maltodextrin, Disodium EDTA, Pentylene Glycol, Carbomer, Rhodiola Rosea Root Extract, Polysorbate 20, Sodium Hyaluronate, Subtilisin, Citronellol, Geraniol. May Contain (+/-): Red 4, Red 33.

Questions or comments?

Call , M - F 8am - 5pm CST. 1-888-704-3440